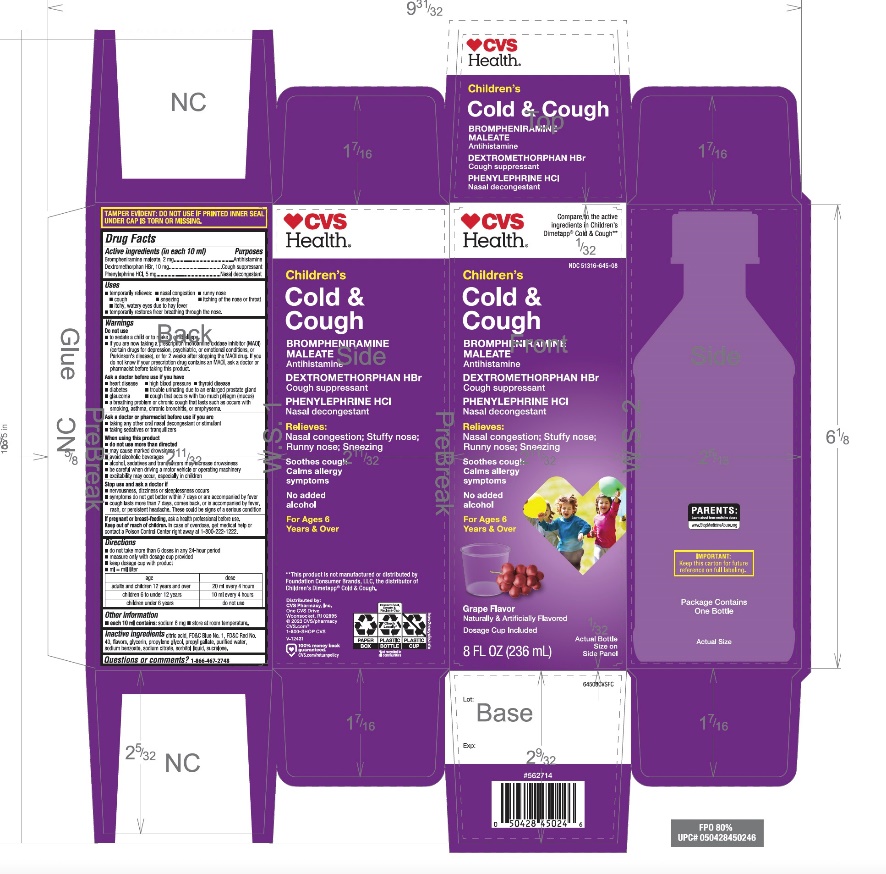 DRUG LABEL: CHILDRENS DIMETAPP COLD AND COUGH
NDC: 51316-645 | Form: LIQUID
Manufacturer: CVS PHARMACY
Category: otc | Type: HUMAN OTC DRUG LABEL
Date: 20251209

ACTIVE INGREDIENTS: BROMPHENIRAMINE MALEATE 2 mg/10 mL; DEXTROMETHORPHAN HYDROBROMIDE 10 mg/10 mL; PHENYLEPHRINE HYDROCHLORIDE 5 mg/10 mL
INACTIVE INGREDIENTS: ANHYDROUS CITRIC ACID; FD&C BLUE NO. 1; FD&C RED NO. 40; GLYCERIN; PROPYLENE GLYCOL; PROPYL GALLATE; WATER; SODIUM BENZOATE; SODIUM CITRATE, UNSPECIFIED FORM; SORBITOL; SUCRALOSE

CVS Children’s Cold & Cough Drug Facts

Active ingredients (in each 10 ml)

Brompheniramine maleate, 2 mg

Dextromethorphan HBr, 10 mg

Phenylephrine HCl , 5 mg

Purposes

Antihistamine

Cough suppressant

Nasal decongestant

Uses

- temporarily relieves:
- Nasal congestion
  - runny nose
  - cough
  - sneezing
  - itchy, watery eyes due to hay fever
  - itching of the nose or throat
- temporarily restores freer breathing through the nose

Warnings

Do not use

- to sedate a child or to make a child sleepy
- if you are now taking a prescription monoamine oxidase inhibitor (MAOI) (certain drugs for depression, psychiatric, or emotional conditions, or Parkinson's disease), or for 2 weeks after stopping the MAOI drug. If you do not know if your prescription drug contains an MAOI, ask a doctor or pharmacist before taking this product.

Ask a doctor before use if you have

- heart disease
- high blood pressure
- thyroid disease
- diabetes
- trouble urinating due to an enlarged prostate gland
- glaucoma
- cough that occurs with too much phlegm (mucus)
- a breathing problem or persistent or chronic cough that lasts such as occurs with smoking, asthma, chronic bronchitis, or emphysema

Ask a doctor or pharmacist before use if you are

- taking any other oral nasal decongestant or stimulant
- taking sedatives or tranquilizers

When using this product

- do not use more than directed
- may cause marked drowsiness
- avoid alcoholic beverages
- alcohol, sedatives, and tranquilizers may increase drowsiness
- be careful when driving a motor vehicle or operating machinery
- excitability may occur, especially in children

Stop use and ask a doctor if

- nervousness, dizziness, or sleeplessness occurs
- symptoms do not get better within 7 days or are accompanied by fever, rash, or persistent headache. These could be signs of a serious condition.

If pregnant or breast-feeding,

ask a health professional before use.

Keep out of reach of children.

In case of overdose, get medical help or contact a Poison Control Center right away at 1-800-222-1222.

Directions

- do not take more than 6 doses in any 24-hour period
- measure only with dosage cup provided
- keep dosage cup with product
- ml = milliliter

age | dose
adults and children 12 years and over | 20 ml every 4 hours
children 6 to under 12 years | 10 ml every 4 hours
children under 6 years | do not use

Other information

- each 10 ml contains: sodium 6 mg
- store at room temperature.

INACTIVE INGREDIENTS

anhydrous citric acid, FD&C blue no. 1, FD&C red no. 40, artificial flavor, glycerin, propylene glycol, propyl gallate, purified water, sodium benzoate, sodium citrate, sorbitol solution, sucralose

Questions or comments?

1-866-467-2748

PRINCIPAL DISPLAY PANEL

Compare to the active ingredients in Children’s Dimetapp® Cold & Cough*

NDC 51316-645-08

Children's

Cold
& Cough

Brompheniramine maleate(Antihistamine)
Dextromethorphan HBr(Cough Suppressant)
Phenylephrine HCl(Nasal Decongestant)

Relieves Nasal Symptoms

- Stuffy Nose
- Runny Nose
- Sneezing

Plus Other Symptoms

- Itchy, Watery Eyes
- Cough

For Ages 6 Years and Over

Grape Flavor

Naturally and Artificially Flavored

8 FL OZ (236 ml)

Distributed by:

*This product is not distributed by Foundation Consumer Brands, LLC, the distributor of Children’s Dimetapp® Cold & Cough*.